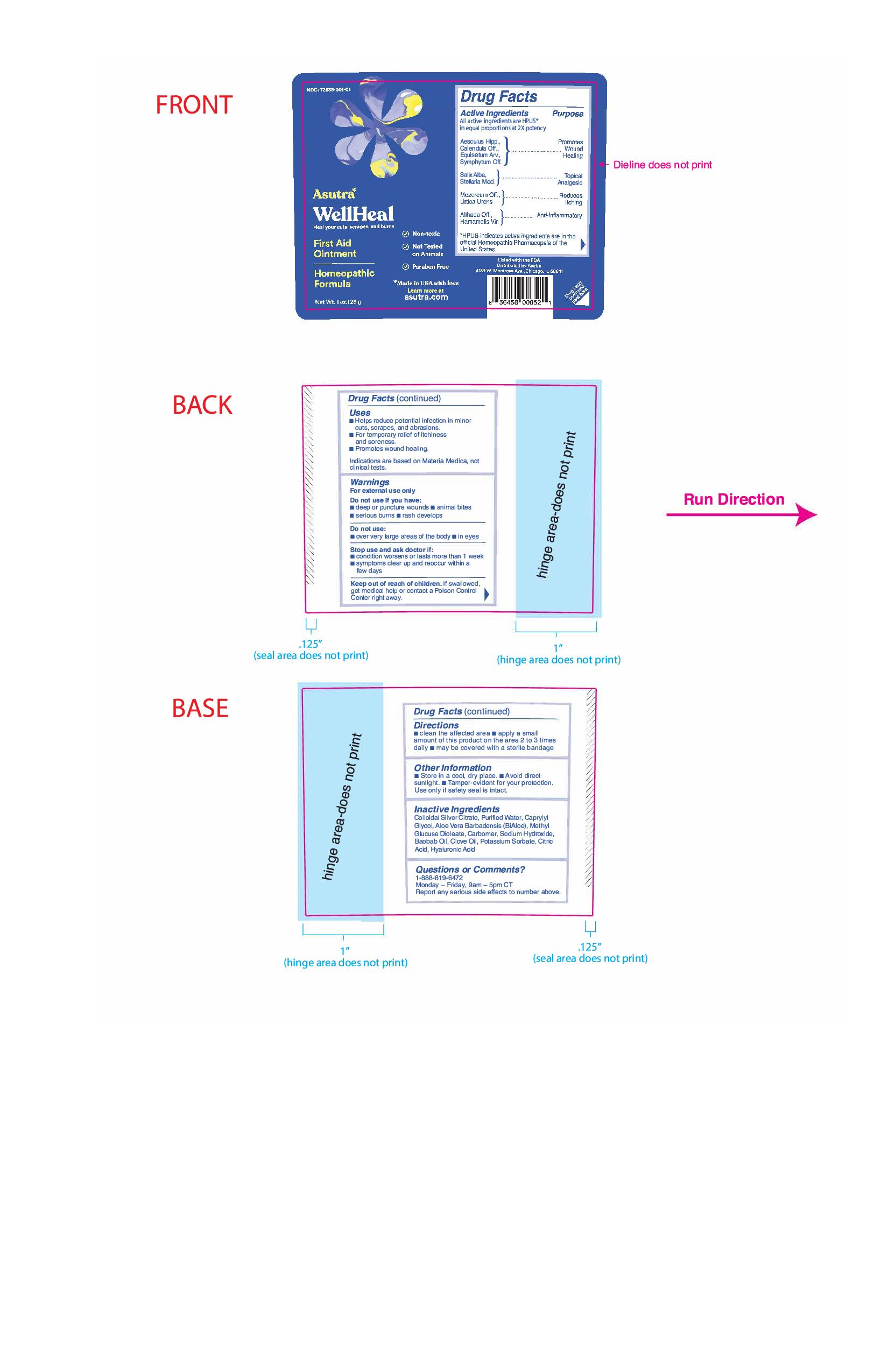 DRUG LABEL: WellHeal
NDC: 72683-001 | Form: CREAM
Manufacturer: Proximity Capital Partners LLC dba Asutra
Category: homeopathic | Type: HUMAN OTC DRUG LABEL
Date: 20201207

ACTIVE INGREDIENTS: EQUISETUM ARVENSE TOP 3 [hp_X]/1 g; SALIX ALBA BARK 3 [hp_X]/1 g; STELLARIA MEDIA 3 [hp_X]/1 g; URTICA URENS 3 [hp_X]/1 g; HORSE CHESTNUT 3 [hp_X]/1 g; COMFREY ROOT 3 [hp_X]/1 g; DAPHNE MEZEREUM BARK 3 [hp_X]/1 g; ALTHAEA OFFICINALIS ROOT 3 [hp_X]/1 g; HAMAMELIS VIRGINIANA ROOT BARK/STEM BARK 3 [hp_X]/1 g; CALENDULA OFFICINALIS FLOWERING TOP 3 [hp_X]/1 g
INACTIVE INGREDIENTS: ALOE VERA LEAF; ADANSONIA DIGITATA SEED OIL; CITRIC ACID MONOHYDRATE; METHYL GLUCOSE DIOLEATE; CARBOXYPOLYMETHYLENE; POTASSIUM SORBATE; WATER; SODIUM HYDROXIDE; CAPRYLYL GLYCOL; CLOVE OIL; SILVER CITRATE; HYALURONIC ACID

ACTIVE INGREDIENT

All active ingredients are HPUS* in equal proportion at 2x potency

Aesculus Hipp., Calendula Off., Equisetum Arv., Symphytum Off.

Salix Alba, Stellaria Med.

Mezereum Off., Urtica Urens

Althaea Off., Hamamelis Vir.

*HPUS indicates active ingredients are in the official Homeopathic Pharmacopeia of the United States.

PURPOSE

All active ingredients are HPUS* in equal proportion at 2x potency

Aesculus Hipp., Calendula Off., Equisetum Arv., Symphytum Off. ................................Promotes Wound Healing

Salix Alba, Stellaria Med. ......................................Topical Analgesic

Mezereum Off., Urtica Urens ................................ Reduces Itching

Althaea Off., Hamamelis Vir. .................................Anti-inflammatory

*HPUS indicates active ingredients are in the official Homeopathic Pharmacopeia of the United States.

INDICATIONS AND USAGE

- Helps reduce potential infection in minor cuts, scrapes, and abrasions.
- For temporary relief of itchiness and soreness.
- Promotes wound healing.

Indications are based on Materia Medica, not clinical tests.

WARNINGS

For external use only.

Do not use if you have:

- deep or puncture wounds
- animal bites
- serious burns
- rash develops

-----

Do not use:

- over large areas of the body
- in eyes

Stop use and ask doctor if:

- condition worsens or lasts more than 1 week
- symptoms clear up and reoccur within a few days

Keep out of reach of children. If swallowed, get medical help or contact a Poisin Control Center right away.

DOSAGE AND ADMINISTRATION

- clean the affected area
- apply a small amount of this product on the area 2 to 3 times daily
- may be covered with a steril bandage

STORAGE AND HANDLING

- Store in a cool, dry place
- Avoid direct sunlight
- Tamper-evident for your protection. Use only if safety seal is intact.

INACTIVE INGREDIENT

Colloidal Silver Citrate, Purified Water, Caprylyl Glycol, Aloe Vera Barbadensis (BiAloe), Methyl Glucose Dioleate, Carbomer, Sodium Hydroxide, Baobab Oil, Clove Oil, Potassium Sorbate, Citric Acid, Hyaluronic Acid

QUESTIONS

1-888-819-6472

Monday - Friday, 9am - 5pm CT

Report any serious side effects to number above.